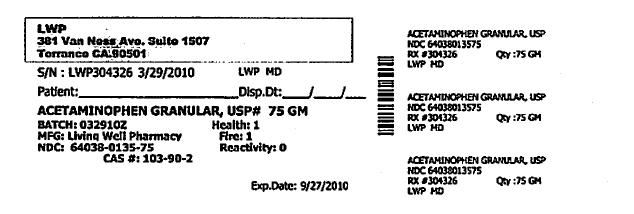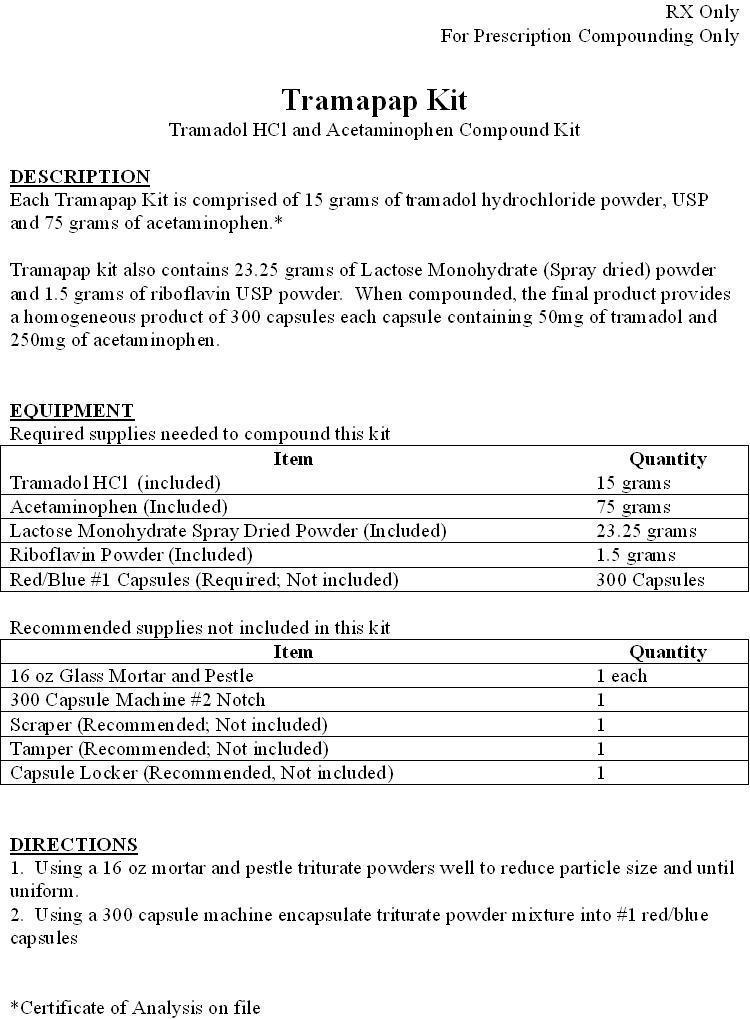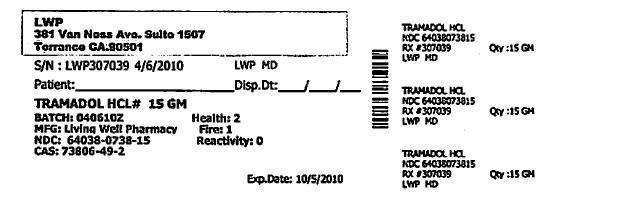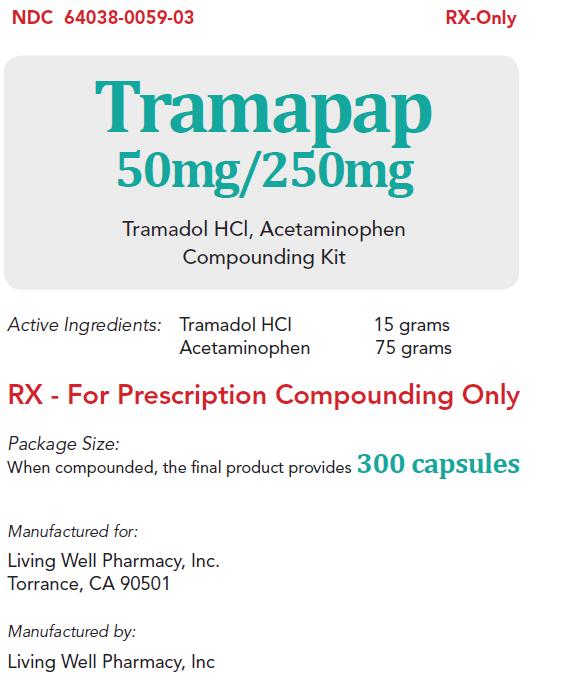 DRUG LABEL: Tramapap
NDC: 64038-059 | Form: KIT | Route: ORAL
Manufacturer: Living Well Pharmacy, Inc.
Category: prescription | Type: HUMAN PRESCRIPTION DRUG LABEL
Date: 20100525

ACTIVE INGREDIENTS: Tramadol Hydrochloride 1 g/1 g; Acetaminophen 1 g/1 g

Tramapap

PACKAGE LABEL

LWP

381 Van Ness Ave. Suite 1507

Torrance CA, 90501

S/N: LWP304326 3/29/2010 LWP,MD

ACETAMINOPHEN GRANULAR, USP #75 GM

BATCH: 03292010Z HEALTH: 1

MFG: LIVING WELL PHARMACY FIRE: 1

NDC: 64038-0135-75 REACTIVITY: 0

CAS #: 103-90-2

PACKAGE LABEL

LWP

381 Van Ness Ave. Suite 1507

Torrance CA, 90501

S/N: LWP307039 4/6/2010 LWP,MD

TRAMADOL HCL #15GM

BATCH: 04062010Z HEALTH: 2

MFG: LIVING WELL PHARMACY FIRE: 1

NDC: 64038-0738-15 REACTIVITY: 0

CAS #: 73806-49-2

DESCRIPTION

1. RX Only

For Prescription Compounding Only

Tramapap Kit
Tramadol HCl and Acetaminophen Compound Kit
Description
Each Tramapap Kit is comprised of 15 grams of tramadol hydrochloride powder and 75 grams of acetaminophen powder.
Certificate of Analysis on File
Tramapap Kit also contains 23.25 grams of Lactose Monohydrate (Spray dried) powder and 1.5 grams of
riboflavin USP powder. When compounded, the final product provides a homogeneous product of 300
capsules each capsule containing 50mg of tramadol and 250mg of acetaminophen.

INDICATIONS AND USAGE

Equipment

Required supplies needed to compound this kit

Equipment
Item | Quantity
Tramadol HCl (Included) | 15 grams
Acetaminophen (Included) | 75 grams
Lactose Monohydrate Spray Dried Powder (Included) | 23.25 grams
Riboflavin Powder (Included) | 1.5 grams
Red/Blue #1 Capsules (Required Not Included) | 300 Capsules

DRUG AND OR LABORATORY TEST INTERACTIONS

Equipment

Recommended supplies not included in this kit

Equipment
Item | Quantity
16 oz Glass Mortar and Pestle | 1 each
300 Capsule Machine Number 2 Notch | 1
Scraper (Recommended Not Included) | 1
Tamper (Recommended Not Included) | 1
Capsule Locker (Recommended Not Included) | 1

Directions

1. Using a 16 oz mortar and pestle triturate powders well to reduce particle size until uniform.

2. Using a 300 capsule machine encapsulate triturate powder mixture into number 1 red/blue capsules

STORAGE AND HANDLING

Prior to compounding, store Tramapap Kit at room temperature. Store the final product at room temperature.

WARNINGS AND PRECAUTIONS

Final product for oral use only. Keep out the reach of children. Compounded product, as dispensed,

is stable for at least 180 days or the time remaining on the expiration date of any given ingredient,

which ever is shorter.